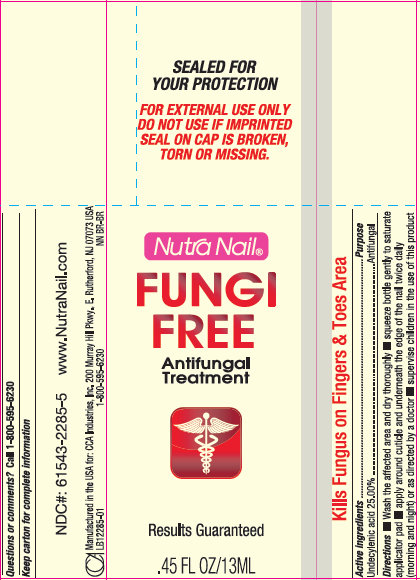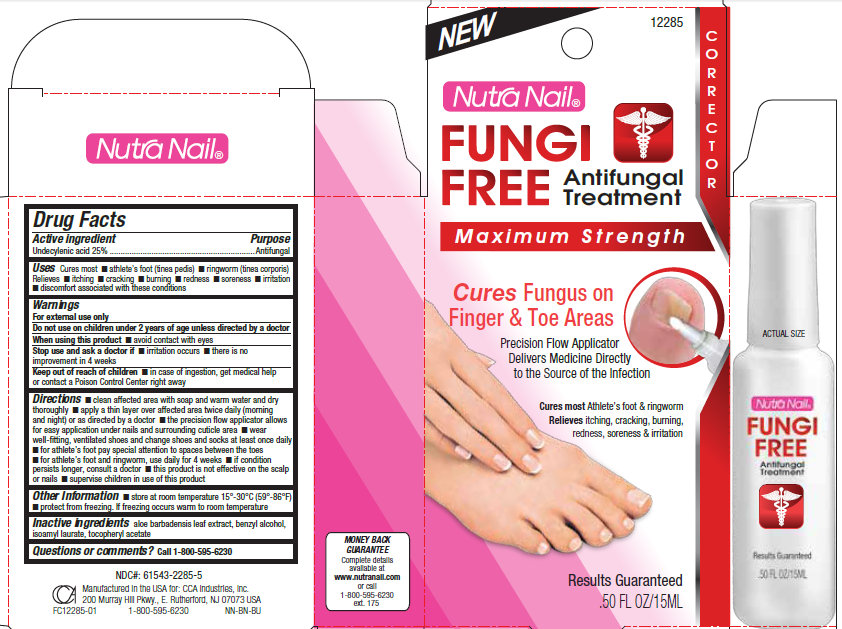 DRUG LABEL: Nutra Nail FUNGI FREE Antifungal Treatment
NDC: 61543-2285 | Form: LIQUID
Manufacturer: CCA Industries, Inc
Category: otc | Type: HUMAN OTC DRUG LABEL
Date: 20140813

ACTIVE INGREDIENTS: UNDECYLENIC ACID 250 mg/1 mL
INACTIVE INGREDIENTS: ALOE VERA LEAF; BENZYL ALCOHOL; ISOAMYL ACETATE; .ALPHA.-TOCOPHEROL ACETATE

Nutra Nail FUNGI FREE Antifungal Treatment

ACTIVE INGREDIENT

Active ingredient / Purpose

Undecylenic acid 25% .................................................................. Antifungal

Uses

Cures most

- athlete's foot (tinea pedis)
- ringworm (tinea corporis)

Relieves

- itching
- cracking
- burning
- redness
- soreness
- irritation
- discomfort associated with these conditions

Warnings

For external use only
Do not use on children under 2 years of age unless directed by a doctor
When using this product

- avoid contact with eyes

Stop use and ask a doctor if

- irritation occurs
- there is no improvement in 4 weeks

Keep out of reach of children

- in case of ingestion, get medical help or contact a Poison Control Center right away

Directions

- clean affected area with soap and warm water and dry thoroughly
- apply a thin layer over affected area twice daily (morning and night) or as directed by a doctor
- the precision flow applicator allows for easy application under nails and surrounding cuticle area
- wear well-fitting, ventilated shoes and change shoes and socks at least once daily
- for athlete's foot pay special attention to spaces between the toes
- for athlete's foot and ringworm, use daily for 4 weeks
- if condition persists longer, consult a doctor
- this product is not effective on the scalp or nails
- supervise children in use of this product

Other Information

- store at room temperature 15 degrees - 30 degrees C (59 degrees - 86 degrees F)
- protect from freezing. If freezing occurs warm to room temperature

Inactive Ingredients

- aloe barbadensis leaf extract, benzyl alcohol, isoamyl laurate, tocopheryl acetate

Questions or comments?

- Call 1-800-595-6230